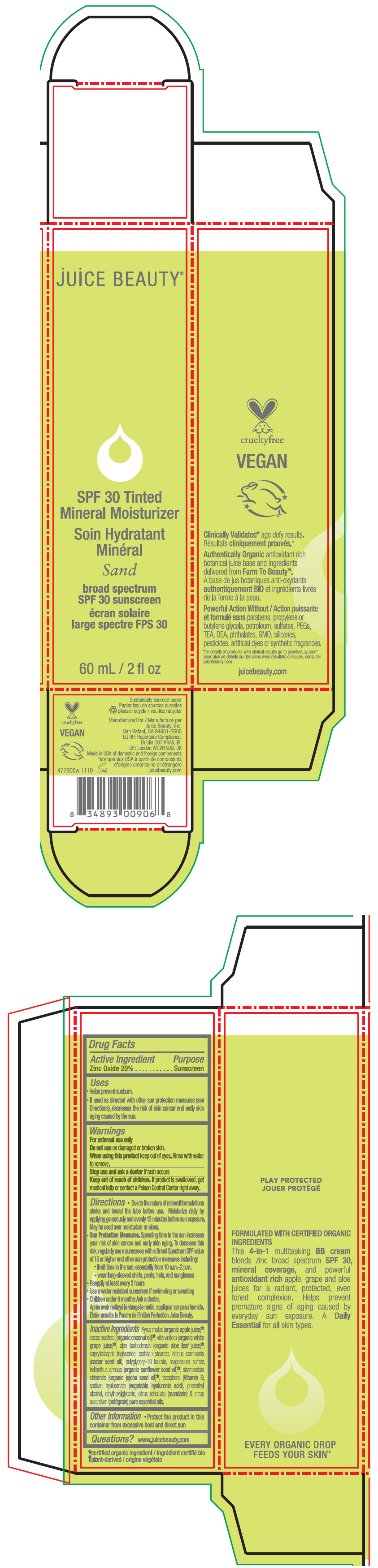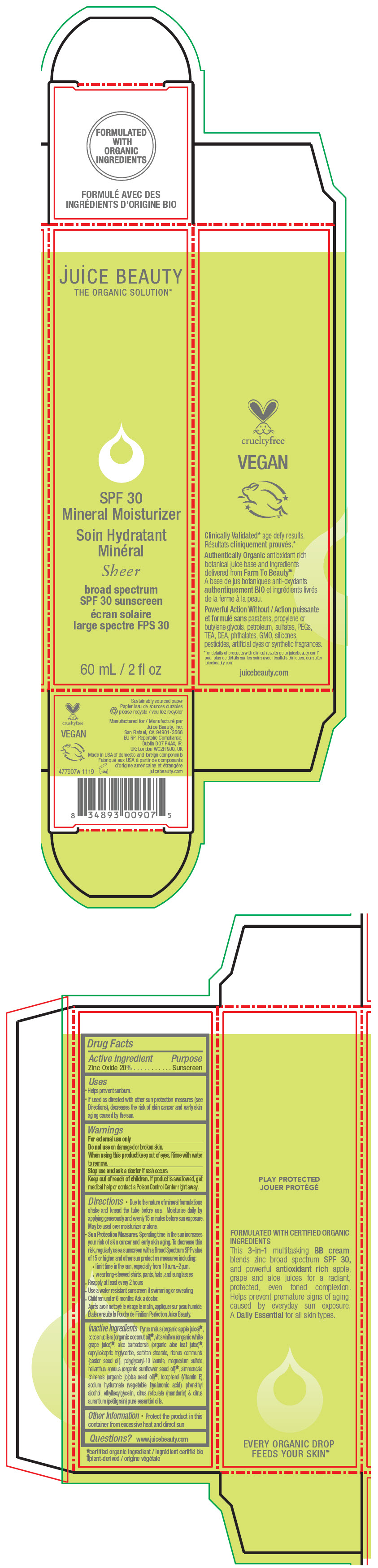 DRUG LABEL: SPF 30 tinted mineral moisturizer Sand
NDC: 55165-0111 | Form: LOTION
Manufacturer: Juice Beauty
Category: otc | Type: HUMAN OTC DRUG LABEL
Date: 20230105

ACTIVE INGREDIENTS: Zinc Oxide 20 g/100 mL
INACTIVE INGREDIENTS: apple juice; grape; aloe vera leaf; coconut oil; medium-chain triglycerides; sorbitan monostearate; castor oil; polyglyceryl-10 laurate; magnesium sulfate, unspecified form; helianthus annuus flowering top; jojoba oil; tocopherol; hyaluronate sodium; phenylethyl alcohol; ethylhexylglycerin; mandarin oil; citrus aurantium leafy twig oil

SPF 30 tinted mineral moisturizer

Drug Facts

Active Ingredient

Zinc Oxide 20%

Purpose

Sunscreen

Uses

- Helps prevent sunburn.
- If used as directed with other sun protection measures (see Directions), decreases the risk of skin cancer and early skin aging caused by the sun.

Warnings

For external use only

Do not use on damaged or broken skin.

When using this product keep out of eyes. Rinse with water to remove.

Stop use and ask a doctor if rash occurs

Keep out of reach of children. If product is swallowed, get medical help or contact a Poison Control Center right away.

Directions

- Due to the nature of mineral formulations shake and knead the tube before use. Moisturize daily by applying generously and evenly 15 minutes before sun exposure. May be used over moisturizer or alone.
- Sun Protection Measures. Spending time in the sun increases your risk of skin cancer and early skin aging. To decrease this risk, regularly use a sunscreen with a Broad Spectrum SPF value of 15 or higher and other sun protection measures including:
  - limit time in the sun, especially from 10 a.m.–2 p.m.
  - wear long-sleeved shirts, pants, hats, and sunglasses
- Reapply at least every 2 hours
- Use a water resistant sunscreen if swimming or sweating
- Children under 6 months: Ask a doctor.

Inactive Ingredients

Pyrus malus (organic apple juice) [certified organic ingredient] , cocos nucifera (organic coconut oil), vitis vinifera (organic white grape juice), aloe barbadensis (organic aloe leaf juice), caprylic/capric triglyceride, sorbitan stearate, ricinus communis (castor seed oil), polyglyceryl-10 laurate, magnesium sulfate, helianthus annuus (organic sunflower seed oil), simmondsia chinensis (organic jojoba seed oil), tocopherol (Vitamin E), sodium hyaluronate (vegetable hyaluronic acid), phenethyl alcohol, ethylhexylglycerin, citrus reticulata (mandarin) & citrus aurantium (petitgrain) pure essential oils.

Other Information

- Protect the product in this container from excessive heat and direct sun

Questions?

www.juicebeauty.com

PRINCIPAL DISPLAY PANEL - 60 mL Tube Carton - Sand

juice BEAUTY®

SPF 30 Tinted
Mineral Moisturizer

Sand

broad spectrum
SPF 30 sunscreen

60 mL / 2 fl oz

PRINCIPAL DISPLAY PANEL - 60 mL Tube Carton - Sheer

juice BEAUTY
THE ORGANIC SOLUTION™

SPF 30
Mineral Moisturizer

Sheer

broad spectrum
SPF 30 sunscreen

60 mL / 2 fl oz